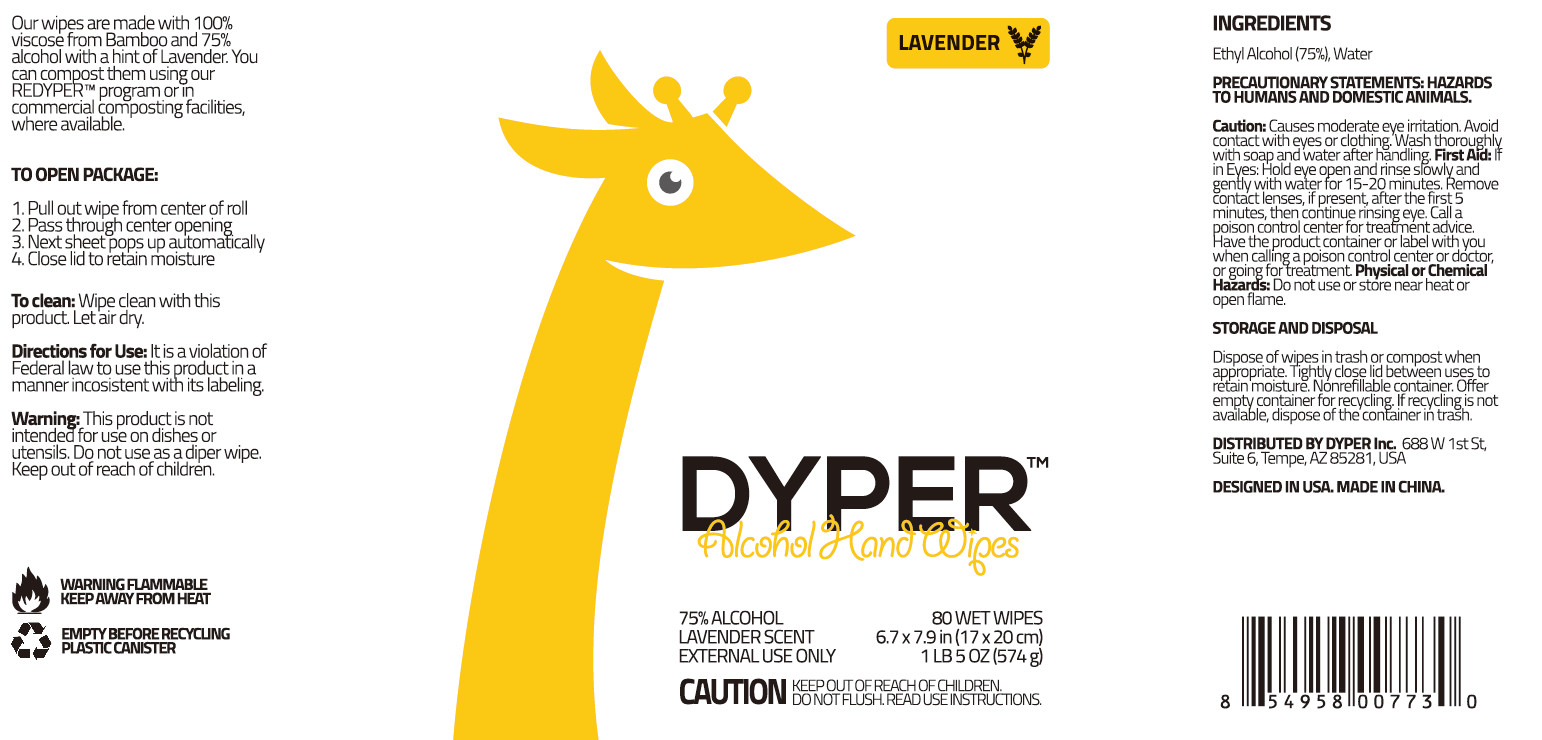 DRUG LABEL: ALCOHOL HAND WIPES
NDC: 55415-004 | Form: CLOTH
Manufacturer: JIANGSU MEIFAN BIOTECHNOLOGY CO., LTD.
Category: otc | Type: HUMAN OTC DRUG LABEL
Date: 20220422

ACTIVE INGREDIENTS: ALCOHOL 270 mL/80 1
INACTIVE INGREDIENTS: FRAGRANCE LAVENDER & CHIA F-153480; WATER

Do not use or store near heat or open flame.

INACTIVE INGREDIENT

SPUNLACE NONWOVEN, PURIFIED WATER, FRAGRANCE

INDICATIONS AND USAGE

1. Pull out wipe from center of roll
2. Pass thraugh center opening
3. Next sheetpops up automatially
4. Close lid to retain moisture

ACTIVE INGREDIENT

ETHYL ALCOHOL

keep out of reach of children

PURPOSE

Disinfection
Sterilization
No Rinseing

WARNINGS

Causes moderate eye imitation. Avoid contact with eyes or clothing. Wash thoroughly with soap andwater after handling. First Aid: if in Eyes: Hold eye open and rinse slowly and gently with water for 15-20 minutes. Remove Contaict lenses, if present, after the first5 minutes, then continue rinsing eye. Call a poison. control center for treafment advice. Have the product container or label with you when calling a poison control center or doctor, or going for treatment Physical or Chemical Hazards: Do not use or store near heat or open flame.